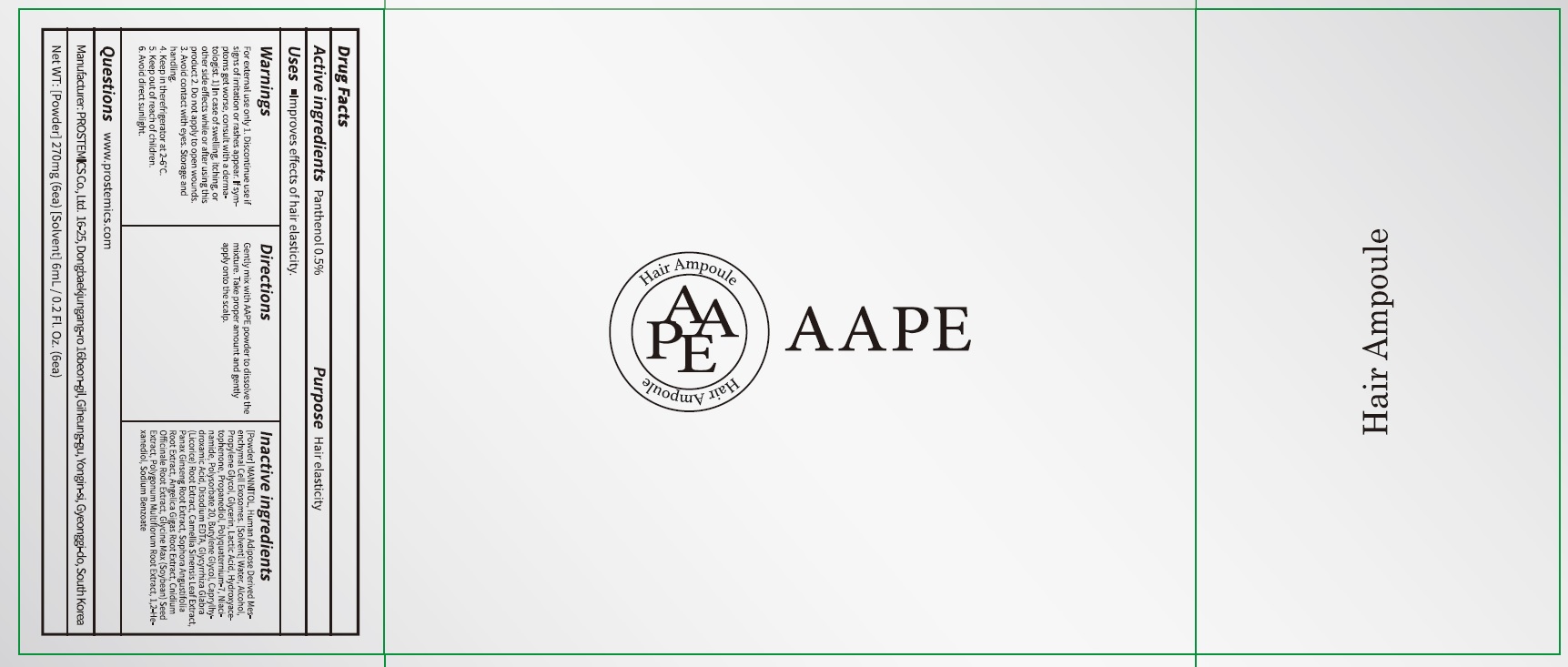 DRUG LABEL: AAPE Hair Ampoule
NDC: 62041-330 | Form: LIQUID
Manufacturer: PROSTEMICS Co., Ltd.
Category: otc | Type: HUMAN OTC DRUG LABEL
Date: 20210528

ACTIVE INGREDIENTS: Panthenol 0.5 g/100 mL
INACTIVE INGREDIENTS: Water; Alcohol

ACTIVE INGREDIENT

Panthenol 0.5%

INACTIVE INGREDIENT

[Powder] MANNITOL, Human Adipose Derived Mesenchymal Cell Exosomes.

[Solvent] Water, Alcohol, Propylene Glycol, Glycerin, Lactic Acid, Hydroxyacetophenone, Propanediol, Polyquaternium-7, Niacinamide, Polysorbate 20, Butylene Glycol, Caprylhydroxamic Acid, Disodium EDTA, Glycyrrhiza Glabra (Licorice) Root Extract, Camellia Sinensis Leaf Extract, Panax Ginseng Root Extract, Sophora Angustifolia Root Extract, Angelica Gigas Root Extract, Cnidium Officinale Root Extract, Glycine Max (Soybean) Seed Extract, Polygonum Multiflorum Root Extract, 1,2-Hexanediol, Sodium Benzoate

PURPOSE

Hair elasticity

WARNINGS

For external use only
1. Discontinue use if signs of irritation or rashes appear. If symptoms get worse, consult with a dermatologist. 1) In case of swelling, itching, or other side effects while or after using this product
2. Do not apply to open wounds.
3. Avoid contact with eyes.
Storage and handling
4. Keep in the refrigerator at 2-6°C.
5. Keep out of reach of children.
6. Avoid direct sunlight.

KEEP OUT OF REACH OF CHILDREN

Uses

■ Improves effects of hair elasticity.

Directions

Gently mix with AAPE powder to dissolve the mixture.
Take proper amount and gently apply onto the scalp

QUESTIONS

www.prostemics.com